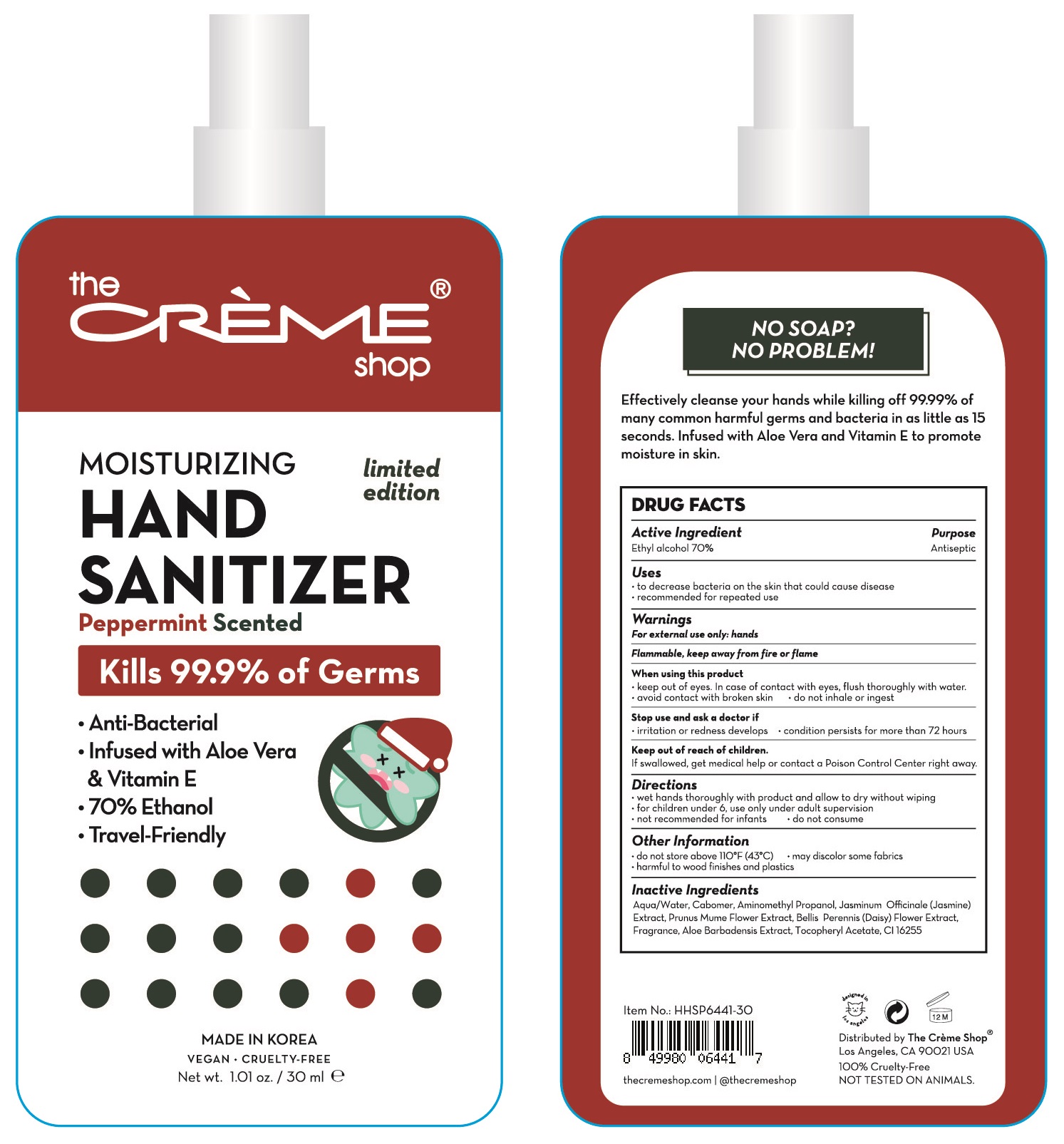 DRUG LABEL: MOISTURIZING HAND SANITIZER Peppermint
NDC: 75010-130 | Form: GEL
Manufacturer: Mirfeel Korea Co., Ltd
Category: otc | Type: HUMAN OTC DRUG LABEL
Date: 20200811

ACTIVE INGREDIENTS: Alcohol 21 mL/30 mL
INACTIVE INGREDIENTS: Water; CARBOMER HOMOPOLYMER, UNSPECIFIED TYPE; AminomethylPropanol; JASMINUM OFFICINALE FLOWER; PRUNUS MUME FLOWER; BELLIS PERENNIS FLOWER; ALOE VERA LEAF; .ALPHA.-TOCOPHEROL ACETATE

ACTIVE INGREDIENT

Ethyl alcohol 70%

INACTIVE INGREDIENT

Aqua/Water, Carbomer, Aminomethyl Propanol, Jasminum Officinale (Jasmine) Extract, Prunus Mume Flower Extract, Bellis Perennis (Daisy) Flower Extract, Fragrance, Aloe Barbadensis Extract, Tocopheryl Acetate, CI 16255

PURPOSE

Antiseptic

WARNINGS

For external use only: hands

--------------------------------------------------------------------------------------------------------

Flammable. Keep away from fire or flame
--------------------------------------------------------------------------------------------------------
When using this product

ㆍkeep out of eyes. In case of contact with eyes, flush thoroughly with water.
ㆍavoid contact with broken skin ㆍdo not inhale or ingest
--------------------------------------------------------------------------------------------------------
Stop use and ask a doctor if

ㆍirritation or redness develops ㆍcondition persists for more than 72 hours

KEEP OUT OF REACH OF CHILDREN

If swallowed, get medical help or contact a Poison Control Center right away.

Uses

ㆍto decrease bacteria on the skin that could cause disease
ㆍrecommended for repeated use

Directions

ㆍwet hands thoroughly with product and allow to dry without wiping
ㆍfor children under 6, use only under adult supervision
ㆍnot recommended for infants
ㆍdo not consume

Other Information

ㆍstore below 110℉ (43℃) ㆍmay discolor some fabrics
ㆍharmful to wood finishes and plastics